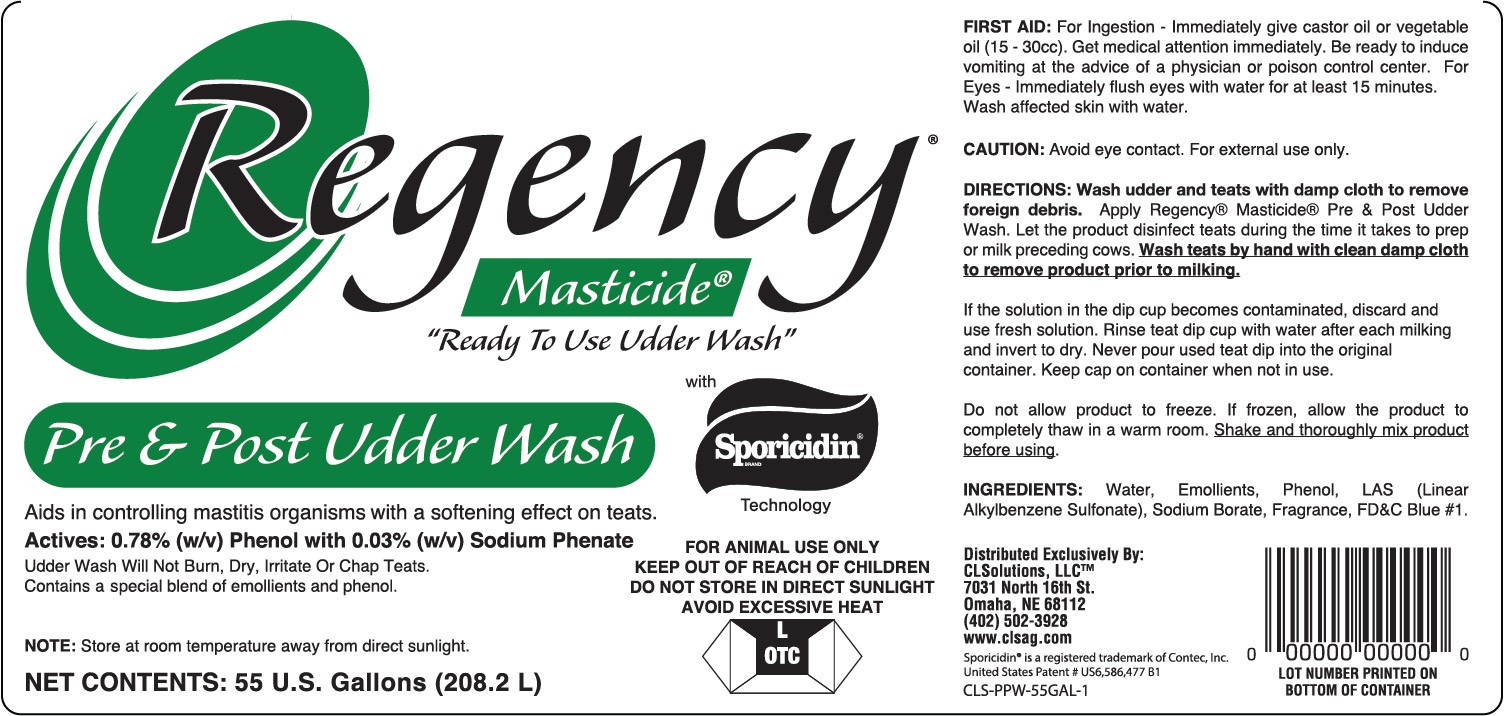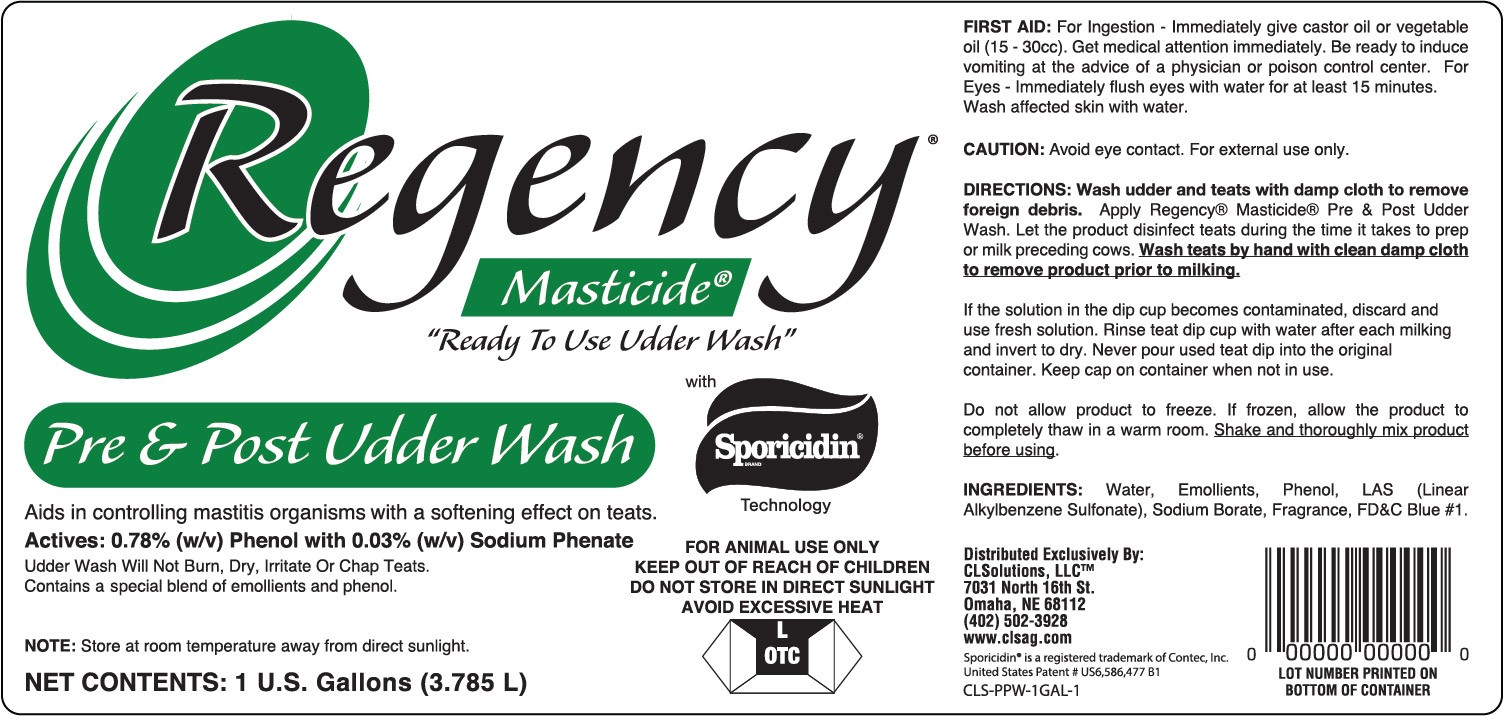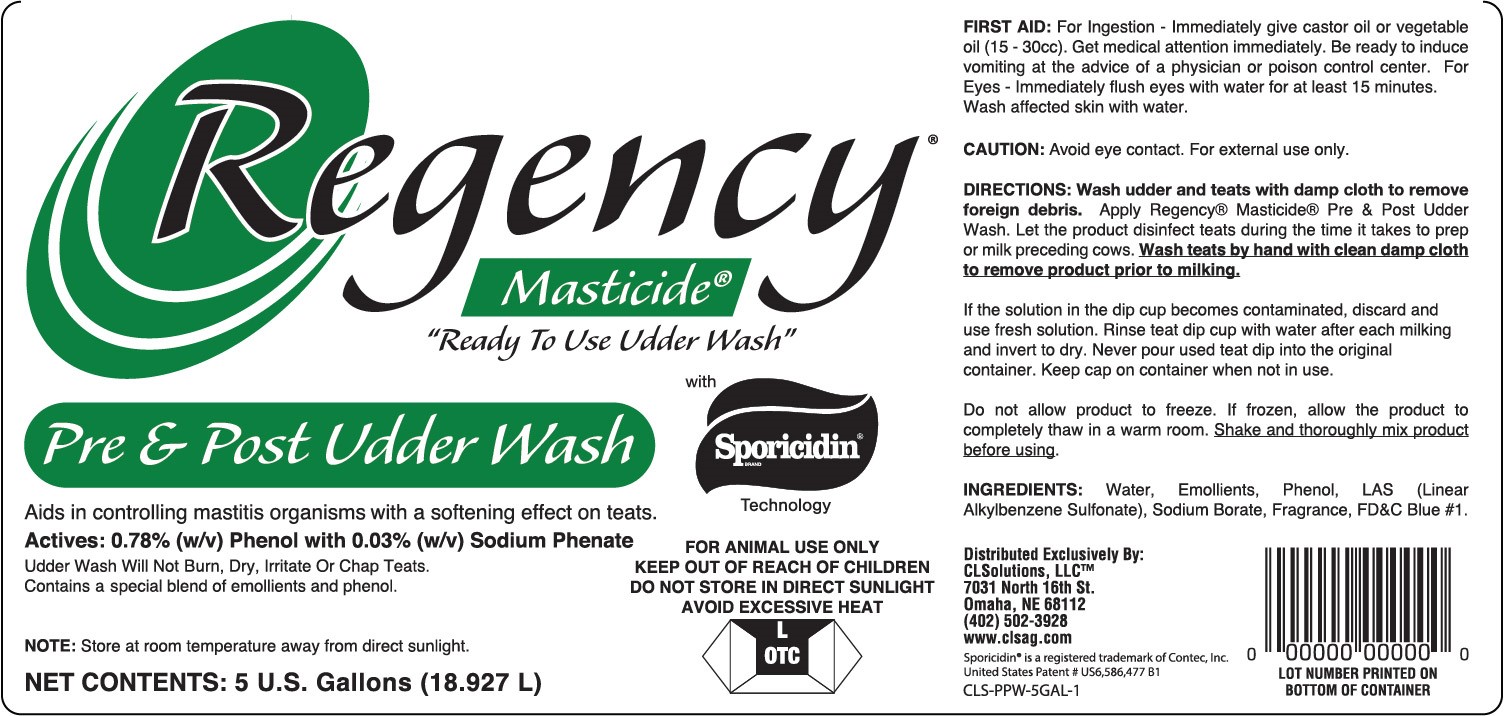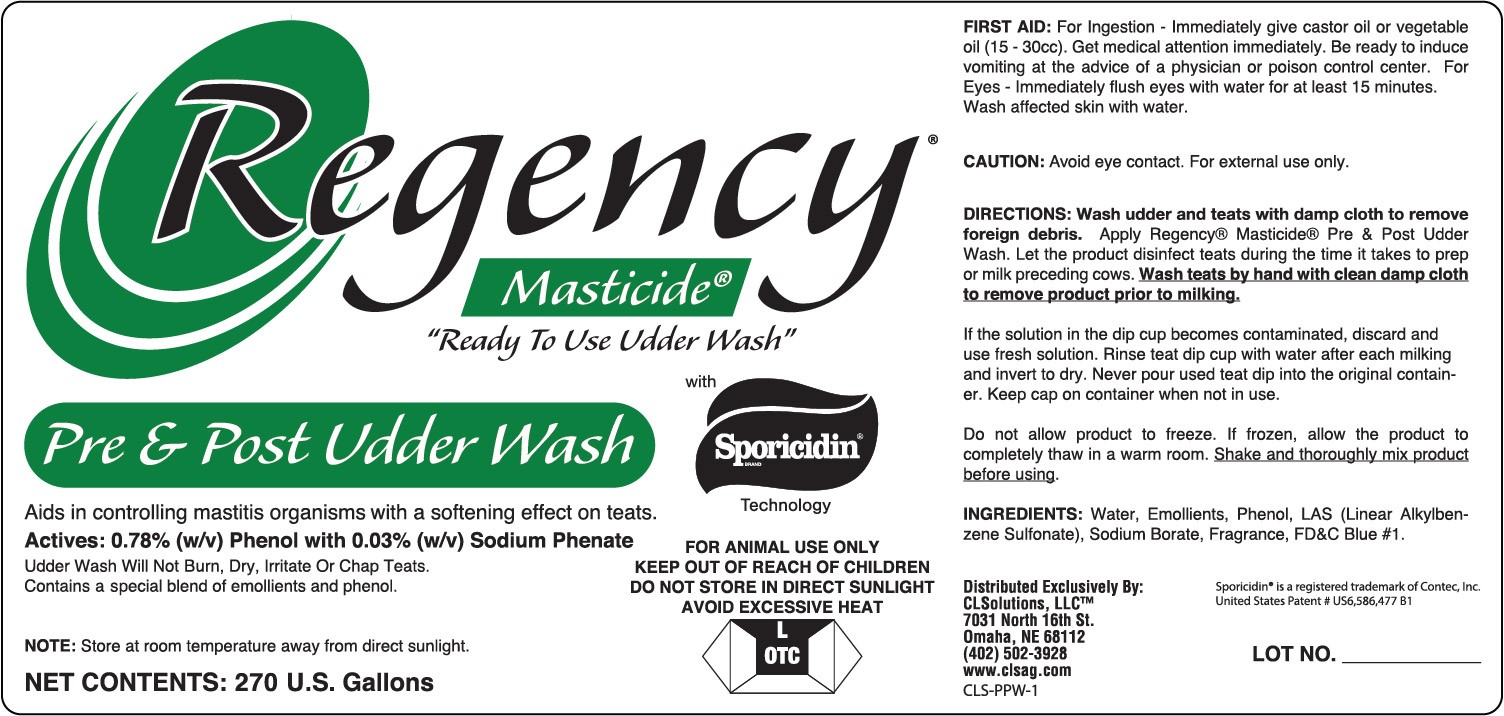 DRUG LABEL: Regency Pre and Post Udder Wash
NDC: 86018-001 | Form: SOLUTION
Manufacturer: CLSolutions
Category: animal | Type: OTC ANIMAL DRUG LABEL
Date: 20171218

ACTIVE INGREDIENTS: PHENOL 78 g/1 L; PHENOLATE SODIUM .03 g/1 L
INACTIVE INGREDIENTS: GLYCERIN; P-DODECYLBENZENESULFONIC ACID; SODIUM BORATE; FD&C BLUE NO. 1; WATER

Regency Pre and Post Udder Wash

ACTIVE INGREDIENTS:

Active Ingredients |  | Purpose
PHENOL (0.78% w/v) |  | Disinfectant
PHENOLATE SODIUM (0.03% w/v) |  | Disinfectant

PURPOSE:

Active Ingredients |  | Purpose
PHENOL (0.78% w/v) |  | Disinfectant
PHENOLATE SODIUM (0.03% w/v) |  | Disinfectant

Keep Out of Reach of Children.

If swallowed, get medical help or contact Poison Control Center right away.

USES:

FOR ANIMAL USE ONLY

Aids in controlling mastitis organisms with a softening effect on teats

Directions for Use:

Wash udder and teats with damp cloth to remove foreign debris.

Apply 0.5X Pre-Milking Teat Dip.

Allow product to disinfect teats during the time it takes to prep or milk preceeding cows.

Wash teats by hand with clean damp cloth to remove product prior to milking.

WARNINGS AND PRECAUTIONS

CAUTION:

Avoid eye contact. For external use only.

FIRST AID:

For Ingestion - Immediately give castor oil or vegetable oil (15-30cc). Get medical attention immediately.

Be ready to induce vomiting at the advice of a physician or poison control center.

For Eyes - Immediately fush eyes with water for at least 15 minutes. Wash affected skin with water.

When using this product:

Do Not Store in Direct Sunlight.

Avoid Excessive Heat.

User Safety Warnings

Do Not Allow Product To Freeze. If frozen, allow the product to completely thaw in a warm room.

Shake and thoroughly mix product before using.

Rinse teat dip cup with water after each milking and invert to dry.

Never pour used teat dip into original container.

Keep cap on container when not in use.

INACTIVE INGREDIENTS:

Water, Glycerin, Linear Alkylbenzene Sulfonate, Sodium Borate, Fragrance, FD&C Blue #1

PACKAGE LABEL

Regency Masticide Pre and Post Udder Wash - Ready To Use Udder Wash with Sporicidin Technology

Aids in controlling mastitis organisms with a softening effect on teats.

0.78% (w/v) Phenol with 0.03% (w/v) Sodium Phenate

Teat Dip Will Not Burn, Dry, Irritate or Chap Teats. Contains special blend of emollients and phenol.

NET CONTENTS: 270 U.S. Gallons

PACKAGE LABEL

Regency Masticide Pre and Post Udder Wash - Ready To Use Udder Wash with Sporicidin Technology

Aids in controlling mastitis organisms with a softening effect on teats.

0.78% (w/v) Phenol with 0.03% (w/v) Sodium Phenate

Teat Dip Will Not Burn, Dry, Irritate or Chap Teats. Contains special blend of emollients and phenol.

NET CONTENTS: 55 Gallons (208.2 L)

PACKAGE LABEL

Regency Masticide Pre and Post Udder Wash - Ready To Use Udder Wash with Sporicidin Technology

Aids in controlling mastitis organisms with a softening effect on teats.

0.78% (w/v) Phenol with 0.03% (w/v) Sodium Phenate

Teat Dip Will Not burn, Dry, Irritate or Chap Teats, Contains a special blend of emollients and phenol.

NET CONTENTS: 5 U.S. Gallons (18.927 L)

PACKAGE LABEL

Regency Masticide Pre and Post Udder Wash - Ready To Use Udder Wash with Sporicidin Technology

Aids in controlling mastitis organisms with a softening effect on teats.

0.78% (w/v) Phenol with 0.03% (w/v) Sodium Phenate

Teat Dip Will Not burn, Dry, Irritate or Chap Teats, Contains a special blend of emollients and phenol.

NET CONTENTS: 1 U.S. Gallons (3.785 L)